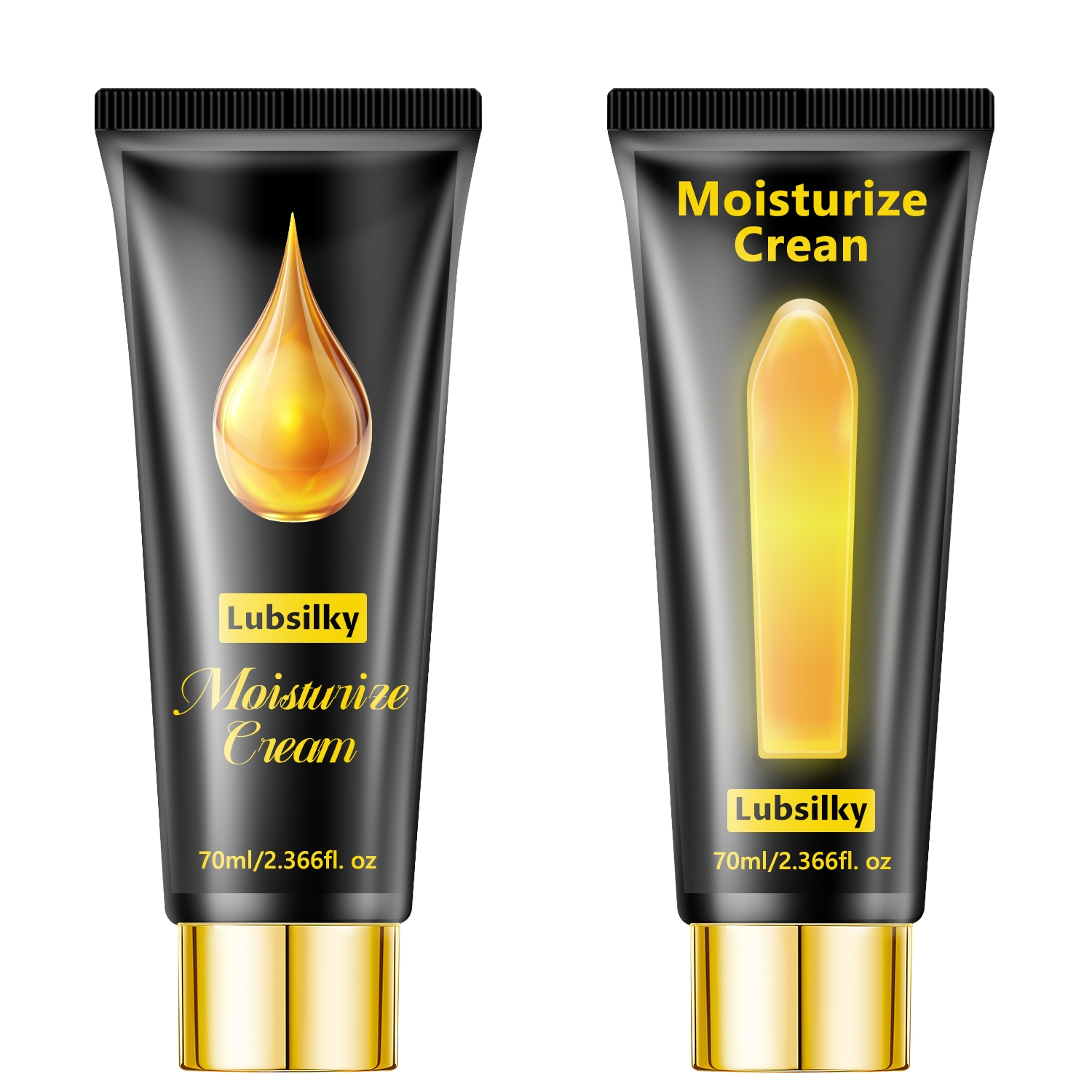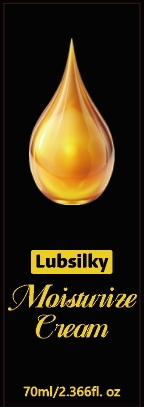 DRUG LABEL: Moisturize Cream
NDC: 84025-302 | Form: CREAM
Manufacturer: Guangzhou Yanxi Biotechnology Co., Ltd
Category: otc | Type: HUMAN OTC DRUG LABEL
Date: 20250104

ACTIVE INGREDIENTS: GLYCERIN 3 mg/70 mL; NIACINAMIDE 5 mg/70 mL
INACTIVE INGREDIENTS: WATER

DOSAGE AND ADMINISTRATION

So easy to use, simply apply the appropriate amount of breast enhancement to a clean, private area and gently massage into ful absorption

INACTIVE INGREDIENT

Aqua

INDICATIONS AND USAGE

For daily skin care

WARNINGS

Keep out of children

Keep out of children

PURPOSE

Skin absorbs it easily, leaving skinhydrated, smooth, Deep moisturizing and nourishing skin, nongreasy, no sticky residue